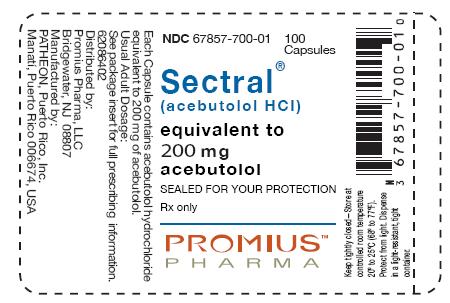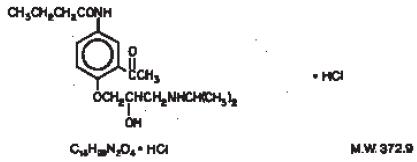 DRUG LABEL: SECTRAL
NDC: 67857-700 | Form: CAPSULE
Manufacturer: Promius Pharma, LLC
Category: prescription | Type: HUMAN PRESCRIPTION DRUG LABEL
Date: 20120112

ACTIVE INGREDIENTS: ACEBUTOLOL HYDROCHLORIDE 200 mg/1 1
INACTIVE INGREDIENTS: D&C Red No. 22; FD&C Blue No. 1; FD&C Yellow No. 6; D&C Red No. 28; gelatin; povidone; starch, corn; stearic acid; titanium dioxide

DESCRIPTION

Sectral (acebutolol HCl) is a selective, hydrophilic beta-adrenoreceptor blocking agent with mild intrinsic sympathomimetic activity for use in treating patients with hypertension and ventricular arrhythmias. It is marketed in capsule form for oral administration. Sectral capsules are provided in two dosage strengths which contain 200 or 400 mg of acebutolol as the hydrochloride salt. The inactive ingredients present are D&C Red 22, FD&C Blue 1, FD&C Yellow 6, gelatin, povidone, starch, stearic acid, and titanium dioxide. The 200 mg dosage strength also contains D&C Red 28 and the 400 mg dosage strength also contains FD&C Red 40.

Acebutolol HCl has the following structural formula:

Acebutolol HCl is a white or slightly off-white powder freely soluble in water, and less soluble in alcohol. Chemically it is defined as the hydrochloride salt of (±)N-[3-Acetyl-4-[2- hydroxy-3-[(1-methylethyl)amino]propoxy]phenyl] butanamide.

CLINICAL PHARMACOLOGY

Sectral is a cardioselective, β-adrenoreceptor blocking agent, which possesses mild intrinsic sympathomimetic activity (ISA) in its therapeutically effective dose range.

Pharmacodynamics

β1-cardioselectivity has been demonstrated in experimental animal studies. In anesthetized dogs and cats, Sectral is more potent in antagonizing isoproterenol-induced tachycardia (β1) than in antagonizing isoproterenol-induced vasodilatation (β2).In guinea pigs and cats, it is more potent in antagonizing this tachycardia than in antagonizing isoproterenol- induced bronchodilatation (β2). ISA of Sectral has been demonstrated in catecholamine-depleted rats by tachycardia induced by intravenous administration of this agent. A membrane-stabilizing effect has been detected in animals, but only with high concentrations of Sectral.

Clinical studies have demonstrated β1-blocking activity at the recommended doses by: a) reduction in the resting heart rate and decrease in exercise-induced tachycardia; b) reduction in cardiac output at rest and after exercise; c) reduction of systolic and diastolic blood pressures at rest and postexercise; d) inhibition of isoproterenol-induced tachycardia.

The β1-selectivity of Sectral has also been demonstrated on the basis of the following vascular and bronchial effects:

Vascular Effects: Sectral has less antagonistic effects on peripheral vascular β2-receptors at rest and after epinephrine stimulation than nonselective β-antagonists.

Bronchial Effects: In single-dose studies in asthmatics examining effects of various beta-blockers on pulmonary function, low doses of acebutolol produce less evidence of bronchoconstriction and less reduction of beta2 agonist, bronchodilating effects, than nonselective agents like propranolol but more than atenolol.

ISA has been observed with Sectral in man, as shown by a slightly smaller (about 3 beats per minute) decrease in resting heart rate when compared to equivalent β-blocking doses of propranolol, metoprolol or atenolol. Chronic therapy with Sectral induced no significant alteration in the blood lipid profile.

Sectral has been shown to delay AV conduction time and to increase the refractoriness of the AV node without significantly affecting sinus node recovery time, atrial refractory period, or the HV conduction time. The membrane-stabilizing effect of Sectral is not manifest at the doses used clinically.

Significant reductions in resting and exercise heart rates and systolic blood pressures have been observed 1.5 hours after Sectral administration with maximal effects occurring between 3 and 8 hours postdosing in normal volunteers. Sectral has demonstrated a significant effect on exercise-induced tachycardia 24 to 30 hours after drug administration.

There are significant correlations between plasma levels of acebutolol and both the reduction in resting heart rate and the percent of β-blockade of exercise-induced tachycardia.

The antihypertensive effect of Sectral has been shown in double-blind controlled studies to be superior to placebo and similar to propranolol and hydrochlorothiazide. In addition, patients responding to Sectral administered twice daily had a similar response whether the dosage regimen was changed to once daily administration or continued on a b.i.d. regimen. Most patients responded to 400 to 800 mg per day in divided doses.

The antiarrhythmic effect of Sectral was compared with placebo, propranolol, and quinidine. Compared with placebo, Sectral significantly reduced mean total ventricular ectopic beats (VEB), paired VEB, multiform VEB, R-on-T beats, and ventricular tachycardia (VT). Both Sectral and propranolol significantly reduced mean total and paired VEB and VT. Sectral and quinidine significantly reduced resting total and complex VEB; the antiarrhythmic efficacy of Sectral was also observed during exercise.

Pharmacokinetics and Metabolism

Sectral is well absorbed from the GI tract. It is subject to extensive first-pass hepatic biotransformation, with an absolute bioavailability of approximately 40% for the parent compound. The major metabolite, an N-acetyl derivative (diacetolol), is pharmacologically active. This metabolite is equipotent to Sectral and in cats is more cardioselective than Sectral; therefore, this first-pass phenomenon does not attenuate the therapeutic effect of Sectral. Food intake does not have a significant effect on the area under the plasma concentration-time curve (AUC) of Sectral although the rate of absorption and peak concentration decreased slightly.

The plasma elimination half-life of Sectral is approximately 3 to 4 hours, while that of its metabolite, diacetolol, is 8 to 13 hours. The time to reach peak concentration for Sectral is 2.5 hours and for diacetolol, after oral administration of Sectral, 3.5 hours.

Within the single oral dose range of 200 to 400 mg, the kinetics are dose proportional. However, this linearity is not seen at higher doses, probably due to saturation of hepatic biotransformation sites. In addition, after multiple dosing the lack of linearity is also seen by AUC increases of approximately 100% as compared to single oral dosing. Elimination via renal excretion is approximately 30% to 40% and by nonrenal mechanisms 50% to 60%, which includes excretion into the bile and direct passage through the intestinal wall.

Sectral has a low binding affinity for plasma proteins (about 26%). Sectral and its metabolite, diacetolol, are relatively hydrophilic and, therefore, only minimal quantities have been detected in the cerebrospinal fluid (CSF).

Drug interaction studies with tolbutamide and warfarin indicated no influence on the therapeutic effects of these compounds. Digoxin and hydrochlorothiazide plasma levels were not affected by concomitant Sectral administration. The kinetics of Sectral were not significantly altered by concomitant administration of hydrochlorothiazide, hydralazine, sulfinpyrazone, or oral contraceptives.

In patients with renal impairment, there is no effect on the elimination half-life of Sectral, but there is decreased elimination of the metabolite, diacetolol, resulting in a two- to three-fold increase in its half-life. For this reason, the drug should be administered with caution in patients with renal insufficiency (see PRECAUTIONS). Sectral and its major metabolite are dialyzable.

Sectral crosses the placental barrier and is secreted in breast milk.

In geriatric patients, the bioavailability of Sectral and its metabolite is increased, approximately two-fold, probably due to decreases in the first-pass metabolism and renal function in the elderly.

INDICATIONS AND USAGE

Hypertension

Sectral is indicated for the management of hypertension in adults. It may be used alone or in combination with other antihypertensive agents, especially thiazide-type diuretics.

Ventricular Arrhythmias

Sectral is indicated in the management of ventricular premature beats; it reduces the total number of premature beats, as well as the number of paired and multiform ventricular ectopic beats, and R-on-T beats.

CONTRAINDICATIONS

Sectral is contraindicated in: 1) persistently severe bradycardia; 2) second- and third-degree heart block; 3) overt cardiac failure; and 4) cardiogenic shock. (See WARNINGS.)

WARNINGS

Cardiac Failure

Sympathetic stimulation may be essential for support of the circulation in individuals with diminished myocardial contractility, and its inhibition by β-adrenergic receptor blockade may precipitate more severe failure. Although β-blockers should be avoided in overt cardiac failure, Sectral can be used with caution in patients with a history of heart failure who are controlled with digitalis and/or diuretics. Both digitalis and Sectral impair AV conduction. If cardiac failure persists, therapy with Sectral should be withdrawn.

In Patients Without a History of Cardiac Failure

In patients with aortic or mitral valve disease or compromised left ventricular function, continued depression of the myocardium with β-blocking agents over a period of time may lead to cardiac failure. At the first signs of failure, patients should be digitalized and/or be given a diuretic and the response observed closely. If cardiac failure continues despite adequate digitalization and/or diuretic, Sectral therapy should be withdrawn.

Exacerbation of Ischemic Heart Disease Following Abrupt Withdrawal

Following abrupt cessation of therapy with certain β-blocking agents in patients with coronary artery disease, exacerbation of angina pectoris and, in some cases, myocardial infarction and death have been reported. Therefore, such patients should be cautioned against interruption of therapy without a physician’s advice. Even in the absence of overt ischemic heart disease, when discontinuation of Sectral is planned, the patient should be carefully observed, and should be advised to limit physical activity to a minimum while Sectral is gradually withdrawn over a period of about two weeks. (If therapy with an alternative β-blocker is desired, the patient may be transferred directly to comparable doses of another agent without interruption of β-blocking therapy.) If an exacerbation of angina pectoris occurs, antianginal therapy should be restarted immediately in full doses and the patient hospitalized until his condition stabilizes.

Peripheral Vascular Disease

Treatment with β-antagonists reduces cardiac output and can precipitate or aggravate the symptoms of arterial insufficiency in patients with peripheral or mesenteric vascular disease. Caution should be exercised with such patients, and they should be observed closely for evidence of progression of arterial obstruction.

Bronchospastic Disease

PATIENTS WITH BRONCHOSPASTIC DISEASE SHOULD, IN GENERAL, NOT RECEIVE A β-BLOCKER. Because of its relative β1-selectivity, however, low doses of Sectral may be used with caution in patients with bronchospastic disease who do not respond to, or who cannot tolerate, alternative treatment. Since β1-selectivity is not absolute and is dose-dependent, the lowest possible dose of Sectral should be used initially, preferably in divided doses to avoid the higher plasma levels associated with the longer dose-interval. A bronchodilator, such as theophylline or a β2- stimulant, should be made available in advance with instructions concerning its use.

Anesthesia and Major Surgery

The necessity, or desirability, of withdrawal of a - blocking therapy prior to major surgery is controversial. -adrenergic receptor blockade impairs the ability of the heart to respond to -adrenergically mediated reflex stimuli. While this might be of benefit in preventing arrhythmic response, the risk of excessive myocardial depression during general anesthesia may be enhanced and difficulty in restarting and maintaining the heart beat has been reported with beta-blockers. If treatment is continued, particular care should be taken when using anesthetic agents which depress the myocardium, such as ether, cyclopropane, and trichlorethylene, and it is prudent to use the lowest possible dose of Sectral. Sectral, like other -blockers, is a competitive inhibitor of -receptor agonists, and its effect on the heart can be reversed by cautious administration of such agents (e.g., dobutamine or isoproterenol—see OVERDOSAGE). Manifestations of excessive vagal tone (e.g., profound bradycardia, hypotension) may be corrected

Diabetes and Hypoglycemia

β-blockers may potentiate insulin-induced hypoglycemia and mask some of its manifestations such as tachycardia; however, dizziness and sweating are usually not significantly affected. Diabetic patients should be warned of the possibility of masked hypoglycemia.

Thyrotoxicosis

β-adrenergic blockade may mask certain clinical signs (tachycardia) of hyperthyroidism. Abrupt withdrawal of β-blockade may precipitate a thyroid storm; therefore, patients suspected of developing thyrotoxicosis from whom Sectral therapy is to be withdrawn should be monitored closely.

PRECAUTIONS

GENERAL PRECAUTIONS

Risk of Anaphylactic Reaction

While taking beta-blockers, patients with a history of severe anaphylactic reaction to a variety of allergens may be more reactive to repeated challenge, either accidental, diagnostic, or therapeutic. Such patients may be unresponsive to the usual doses of epinephrine used to treat allergic reaction.

Impaired Renal or Hepatic Function

Studies on the effect of acebutolol in patients with renal insufficiency have not been performed in the U.S. Foreign published experience shows that acebutolol has been used successfully in chronic renal insufficiency. Acebutolol is excreted through the GI tract, but the active metabolite, diacetolol, is eliminated predominantly by the kidney. There is a linear relationship between renal clearance of diacetolol and creatinine clearance. Therefore, the daily dose of acebutolol should be reduced by 50% when the creatinine clearance is less than 50 mL/min and by 75% when it is less than 25 mL/min. Sectral should be used cautiously in patients with impaired hepatic function.

Sectral has been used successfully and without problems in elderly patients in the U.S. clinical trials without specific adjustment of dosage. However, elderly patients may require lower maintenance doses because the bioavailability of both Sectral and its metabolite are approximately doubled in this age group.

Information for Patients

Patients, especially those with evidence of coronary artery disease, should be warned against interruption or discontinuation of Sectral therapy without a physician’s supervision. Although cardiac failure rarely occurs in properly selected patients, those being treated with β-adrenergic blocking agents should be advised to consult a physician if they develop signs or symptoms suggestive of impending CHF, or unexplained respiratory symptoms.

Patients should also be warned of possible severe hypertensive reactions from concomitant use of α-adrenergic stimulants, such as the nasal decongestants commonly used in OTC cold preparations and nasal drops.

Clinical Laboratory Findings

Sectral®, like other β-blockers, has been associated with the development of antinuclear antibodies (ANA). In prospective clinical trials, patients receiving Sectral had a dose-dependent increase in the development of positive ANA titers, and the overall incidence was higher than that observed with propranolol. Symptoms (generally persistent arthralgias and myalgias) related to this laboratory abnormality were infrequent (less than 1% with both drugs). Symptoms and ANA titers were reversible upon discontinuation of treatment.

Drug Interactions:

Catecholamine-depleting drugs, such as reserpine, may have an additive effect when given with β-blocking agents. Patients treated with Sectral plus catecholamine depletors should, therefore, be observed closely for evidence of marked bradycardia or hypotension which may present as vertigo, syncope/presyncope, or orthostatic changes in blood pressure without compensatory tachycardia. Exaggerated hypertensive responses have been reported from the combined use of β-adrenergic antagonists and α-adrenergic stimulants, including those contained in proprietary cold remedies and vasoconstrictive nasal drops. Patients receiving β-blockers should be warned of this potential hazard.

Blunting of the antihypertensive effect of beta-adrenoceptor blocking agents by nonsteroidal anti-inflammatory drugs has been reported.

No significant interactions with digoxin, hydrochlorothiazide, hydralazine, sulfinpyrazone, oral contraceptives, tolbutamide, or warfarin have been observed.

Both digitalis glycosides and beta-blockers slow atrioventricular conduction and decrease heart rate. Concomitant use can increase the risk of bradycardia.

Carcinogenesis, Mutagenesis, Impairment of Fertility:

Chronic oral toxicity studies in rats and mice, employing dose levels as high as 300 mg/kg/day, which is equivalent to 15 times the maximum recommended (60 kg) human dose, did not indicate a carcinogenic potential for Sectral. Diacetolol, the major metabolite of Sectral in man, was without carcinogenic potential in rats when tested at doses as high as 1800 mg/kg/day. Sectral and diacetolol were also shown to be devoid of mutagenic potential in the Ames Test. Sectral, administered orally to two generations of male and female rats at doses of up to 240 mg/kg/day (equivalent to 12 times the maximum recommended therapeutic dose in a 60-kg human) and diacetolol, administered to two generations of male and female rats at doses of up to 1000 mg/kg/day, had no significant impact on reproductive performance or fertility.

Pregnancy

Teratogenic Effects

Pregnancy Category B: Reproduction studies have been performed with Sectral in rats (up to 630 mg/kg/day) and rabbits (up to 135 mg/kg/day). These doses are equivalent to approximately 31.5 and 6.8 times the maximum recommended therapeutic dose in a 60-kg human, respectively. The compound was not teratogenic in either species. In the rabbit, however, doses of 135 mg/kg/day caused slight fetal growth retardation; this effect was considered to be a result of maternal toxicity, as evidenced by reduced food intake, a lowered rate of body weight gain, and mortality. Studies have also been performed in these species with diacetolol (at doses of up to 450 mg/kg/day in rabbits and up to 1800 mg/kg/day in rats). Other than a significant elevation in postimplantation loss with 450 mg/kg/day diacetolol, a level at which food consumption and body weight gain were reduced in rabbit dams and a nonstatistically significant increase in incidence of bilateral cataract in rat fetuses from dams treated with 1800 mg/kg/day diacetolol, there was no evidence of harm to the fetus. There are no adequate and well-controlled trials in pregnant women. Because animal teratology studies are not always predictive of the human response, Sectral should be used during pregnancy only if the potential benefit justifies the risk to the fetus.

Nonteratogenic Effects

Studies in humans have shown that both acebutolol and diacetolol cross the placenta. Neonates of mothers who have received acebutolol during pregnancy have reduced birth weight, decreased blood pressure, and decreased heart rate. In the newborn the elimination half-life of acebutolol was 6 to 14 hours, while the half-life of diacetolol was 24 to 30 hours for the first 24 hours after birth, followed by a half-life of 12 to 16 hours. Adequate facilities for monitoring these infants at birth should be available.

Labor and Delivery

The effect of Sectral on labor and delivery in pregnant women is unknown. Studies in animals have not shown any effect of Sectral on the usual course of labor and delivery.

Nursing Mothers

Acebutolol and diacetolol also appear in breast milk with a milk:plasma ratio of 7.1 and 12.2, respectively. Use in nursing mothers is not recommended.

Pediatric Use

Safety and effectiveness in pediatric patients have not been established.

Geriatric Use

Clinical studies of Sectral and other reported clinical experience is inadequate to determine whether there are differences in safety or effectiveness between patients above or below age 65.

Elderly subjects evidence greater bioavailability of acebutolol (see CLINICAL PHARMACOLOGY—Pharmacokinetics and Metabolism), presumably because of age-related reduction in first-pass metabolism and renal function. Therefore, it may be appropriate to start elderly patients at the low end of the dosing range (see DOSAGE AND ADMINISTRATION—Use in Older Patients).

ADVERSE REACTIONS

Sectral is well tolerated in properly selected patients. Most adverse reactions have been mild, not required discontinuation of therapy, and tended to decrease as duration of treatment increases.

The following table shows the frequency of treatment-related side effects derived from controlled clinical trials in patients with hypertension, angina pectoris, and arrhythmia. These patients received Sectral, propranolol, or hydrochlorothiazide as monotherapy, or placebo.

TOTAL VOLUNTEERED AND ELICITED (U.S. STUDIES)
Body System/ Adverse Reaction | SECTRAL (N=1002) % | Propranolol (N=424) % | Hydrochloro- thiazide (N=178) % | Placebo (N=314) %
Cardiovascular
Chest Pain | 2 | 4 | 4 | 1
Edema | 2 | 2 | 4 | 1
Central Nervous System
Depression | 2 | 1 | 3 | 1
Dizziness | 6 | 7 | 12 | 2
Fatigue | 11 | 17 | 10 | 4
Headache | 6 | 9 | 13 | 4
Insomnia | 3 | 6 | 5 | 1
Abnormal dreams | 2 | 3 | 0 | 1
Dermatologic
Rash | 2 | 2 | 4 | 1
Gastrointestinal
Constipation | 4 | 2 | 7 | 0
Diarrhea | 4 | 5 | 5 | 1
Dyspepsia | 4 | 6 | 3 | 1
Flatulence | 3 | 4 | 7 | 1
Nausea | 4 | 6 | 3 | 0
Genitourinary
Micturition (frequency) | 3 | 1 | 9 | <1
Musculoskeletal
Arthralgia | 2 | 1 | 3 | 2
Myalgia | 2 | 1 | 4 | 0
Respiratory
Cough | 1 | 1 | 2 | 0
Dyspnea | 4 | 6 | 4 | 2
Rhinitis | 2 | 1 | 4 | <1
Special Senses
Abnormal Vision | 2 | 2 | 3 | 0

The following selected (potentially important) side effects were seen in up to 2% of Sectral patients:

Cardiovascular: hypotension, bradycardia, heart failure.

Central Nervous System: anxiety, hyper/hypoesthesia, impotence.

Dermatological: pruritus.

Gastrointestinal: vomiting, abdominal pain.

Genitourinary: dysuria, nocturia.

Liver and Biliary System: A small number of cases of liver abnormalities (increased SGOT, SGPT, LDH) have been reported in association with acebutolol therapy. In some cases increased bilirubin or alkaline phosphatase, fever, malaise, dark urine, anorexia, nausea, headache, and/or other symptoms have been reported. In some of the reported cases, the symptoms and signs were confirmed by rechallenge with acebutolol. The abnormalities were reversible upon cessation of acebutolol therapy.

Musculoskeletal: back pain, joint pain.

Respiratory: pharyngitis, wheezing.

Special Senses: conjunctivitis, dry eye, eye pain.

Autoimmune: In extremely rare instances, systemic lupus erythematosus has been reported.

The incidence of drug-related adverse effects (volunteered and solicited) according to Sectral dose is shown below. (Data from 266 hypertensive patients treated for 3 months on a constant dose.)

Body System | 400 mg/day (N=132) | 800 mg/day (N=63) | 1200 mg/day (N=71)
Cardiovascular | 5% | 2% | 1%
Gastrointestinal | 3% | 3% | 7%
Musculoskeletal | 2% | 3% | 4%
Central Nervous System | 9% | 13% | 17%
Respiratory | 1% | 5% | 6%
Skin | 1% | 2% | 1%
Special Senses | 2% | 2% | 6%
Genitourinary | 2% | 3% | 1%

Potential Adverse Events

In addition, certain adverse effects not listed above have been reported with other β-blocking agents and should also be considered as potential adverse effects of Sectral.

Central Nervous System: Reversible mental depression progressing to catatonia (an acute syndrome characterized by disorientation for time and place), short-term memory loss, emotional lability, slightly clouded sensorium, and decreased performance (neuropsychometrics).

Cardiovascular: Intensification of AV block (see CONTRAINDICATIONS).

Allergic: Erythematous rash, fever combined with aching and sore throat, laryngospasm, and respiratory distress.

Hematologic: Agranulocytosis, nonthrombocytopenic, and thrombocytopenic purpura.

Gastrointestinal: Mesenteric arterial thrombosis and ischemic colitis.

Miscellaneous: Reversible alopecia and Peyronie’s disease. The oculomucocutaneous syndrome associated with the β-blocker practolol has not been reported with Sectral during investigational use and extensive foreign clinical experience.

OVERDOSAGE

No specific information on emergency treatment of overdosage is available for Sectral. However, overdosage with other β-blocking agents has been accompanied by extreme bradycardia, advanced atrioventricular block, intraventricular conduction defects, hypotension, severe congestive heart failure, seizures, and in susceptible patients, bronchospasm and hypoglycemia. Although specific information on the emergency treatment of Sectral overdose is not available, on the basis of the pharmacological actions and the observations in treating overdoses with other β-blockers, the following general measures should be considered:

1. Empty stomach by emesis or lavage.
2. Bradycardia: IV atropine (1 to 3 mg in divided doses). If antivagal response is inadequate, administer isoproterenol cautiously since larger than usual doses of isoproterenol may be required.
3. Persistent hypotension in spite of correction of bradycardia: Administer vasopressor (e.g., epinephrine, levarterenol, dopamine, or dobutamine) with frequent monitoring of blood pressure and pulse rate.
4. Bronchospasm: A theophylline derivative, such as aminophylline and/or parenteral β2-stimulant, such as terbutaline.
5. Cardiac failure: Digitalize the patient and/or administer a diuretic. It has been reported that glucagon is useful in this situation.

Sectral is dialyzable.

DOSAGE AND ADMINISTRATION

Hypertension

The initial dosage of Sectral in uncomplicated mild-to-moderate hypertension is 400 mg. This can be given as a single daily dose, but in occasional patients twice daily dosing may be required for adequate 24-hour blood-pressure control. An optimal response is usually achieved with dosages of 400 to 800 mg per day, although some patients have been maintained on as little as 200 mg per day. Patients with more severe hypertension or who have demonstrated inadequate control may respond to a total of 1200 mg daily (administered b.i.d.), or to the addition of a second antihypertensive agent. Beta-1 selectivity diminishes as dosage is increased.

Ventricular Arrhythmia

The usual initial dose of Sectral is 400 mg daily given as 200 mg b.i.d. Dosage should be increased gradually until an optimal clinical response is obtained, generally at 600 to 1200 mg per day. If treatment is to be discontinued, the dosage should be reduced gradually over a period of about two weeks.

USE IN SPECIFIC POPULATIONS

Use in Older Patients

Older patients have an approximately 2-fold increase in bioavailability and may require lower maintenance doses. Doses above 800 mg/day should be avoided in the elderly.

HOW SUPPLIED

Sectral® (acebutolol HCl) is available in the following dosage strengths:

200 mg, opaque purple and orange capsule marked "RP 700" and "Sectral® 200"
NDC 67857-700-01, in bottles of 100 capsules.

400 mg, opaque brown and orange capsule marked "RP 701" and "Sectral® 400"
NDC 67857-701-01, in bottles of 100 capsules.

Keep tightly closed
Store at controlled room temperature 20° to 25°C (68° to 77°F)
Protect from light
Dispense in a light-resistant, tight container
Use carton to protect contents from light

Distributed by:
Promius Pharma, LLC
Bridgewater, NJ 08807

Manufactured by:
PATHEON, Puerto Rico, Inc.
Manatí, Puerto Rico 00674, USA

Revised April 2008

PRINCIPAL DISPLAY PANEL

NDC-67857-700-01 100 Capsules

SECTRAL®

(acebutolol HCL)

equivalent to
200 mg
acebutolol

SEALED FOR YOUR PROTECTION

Rx only

PROMIUS PHARMA